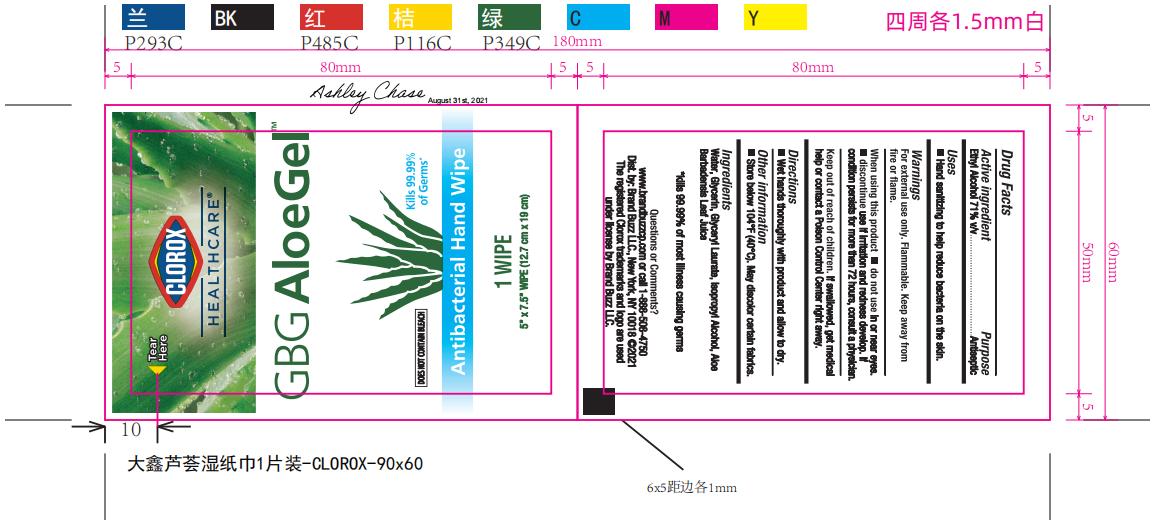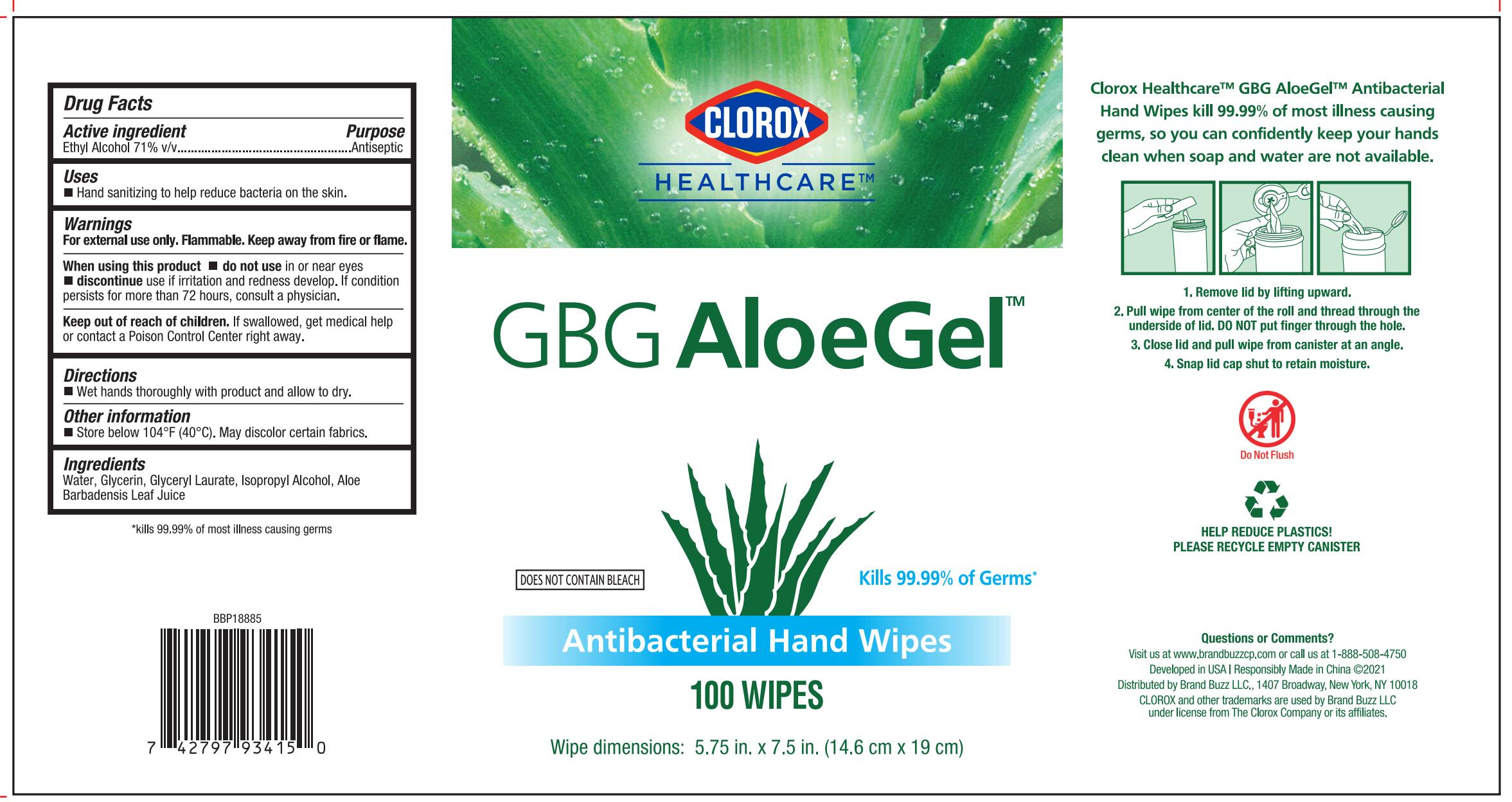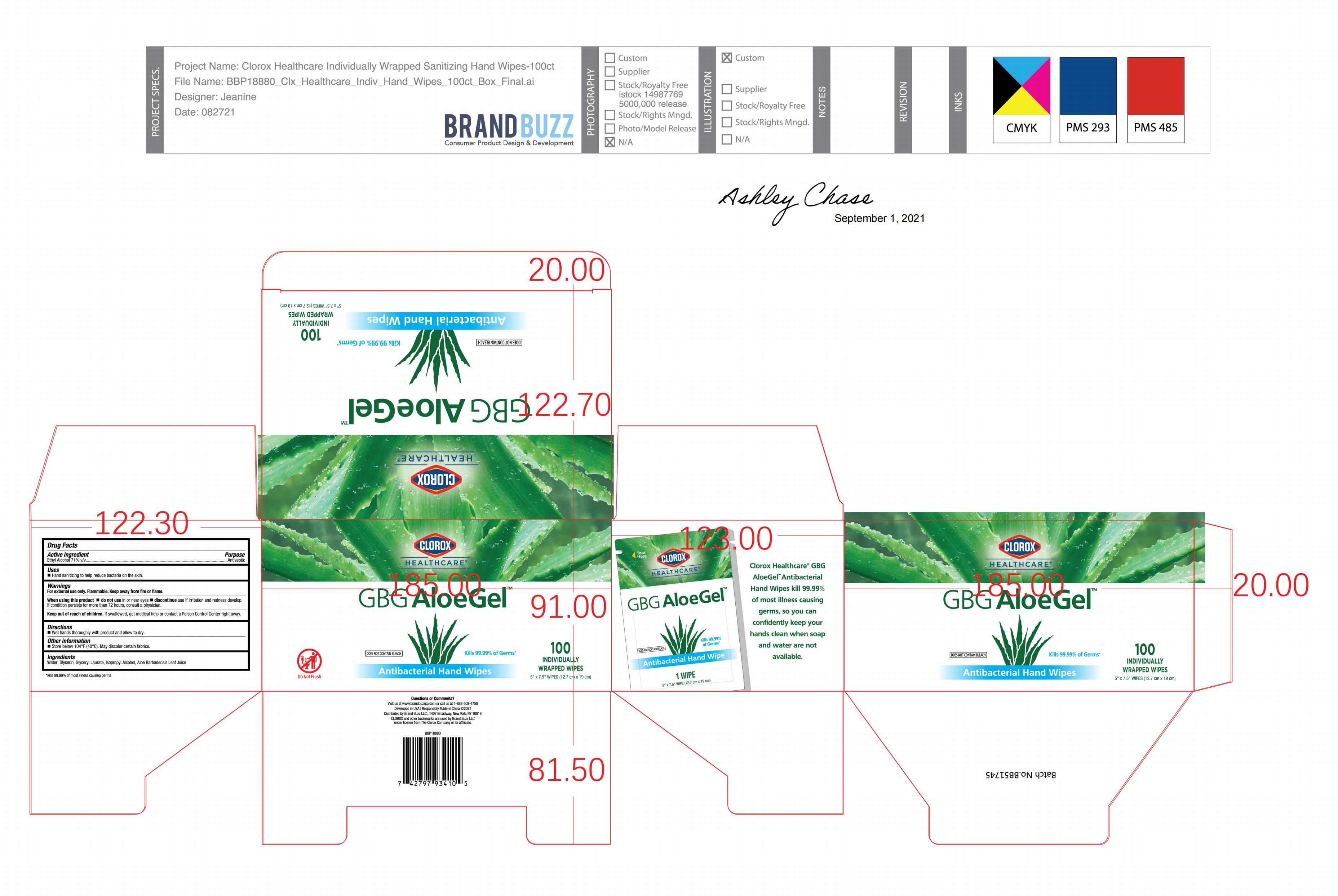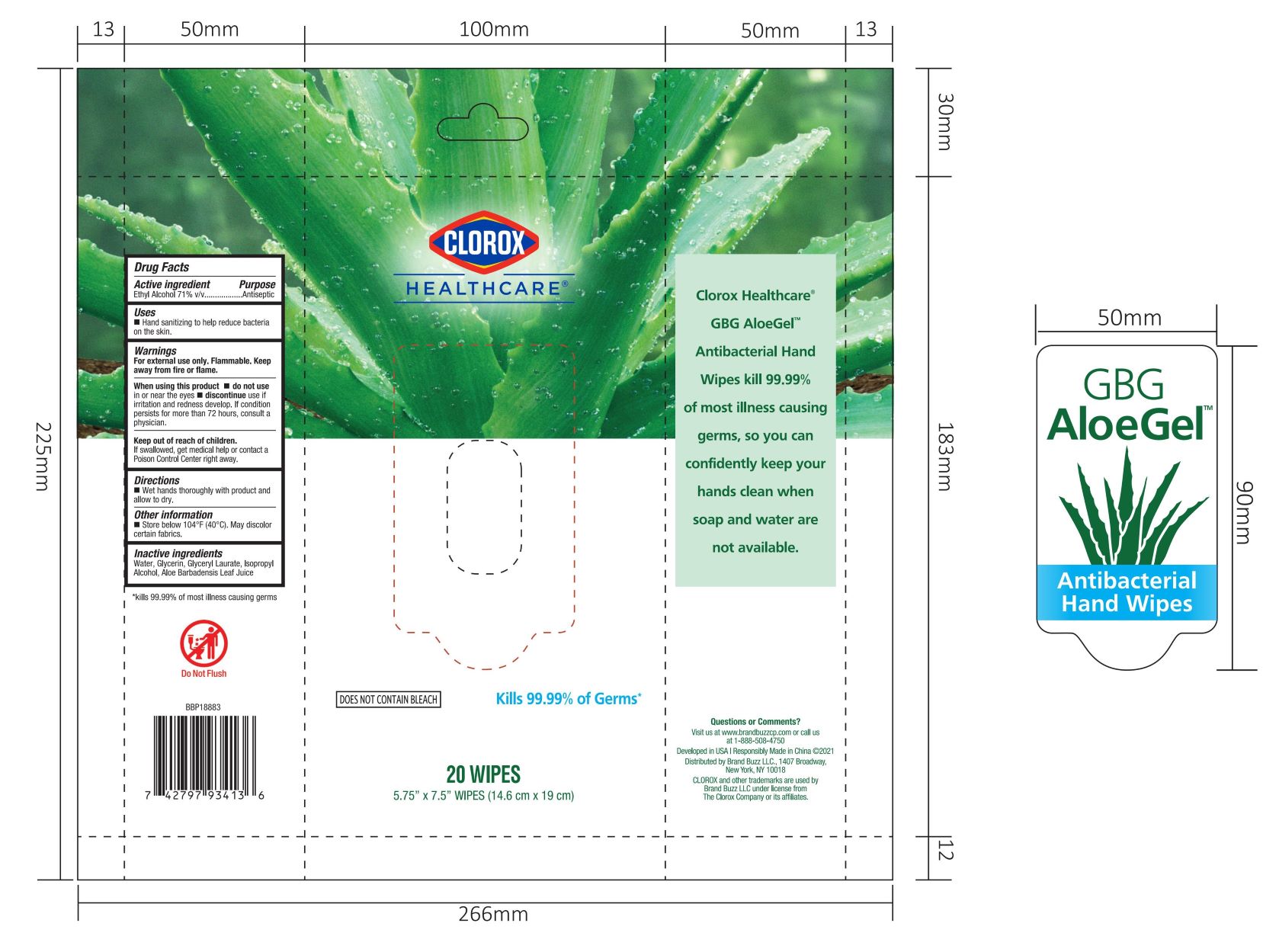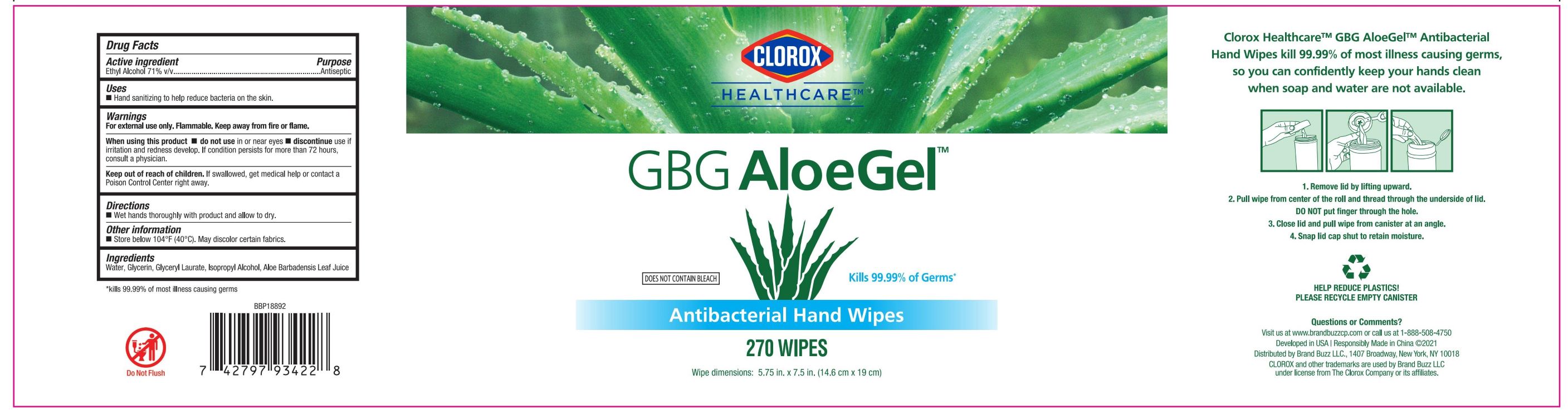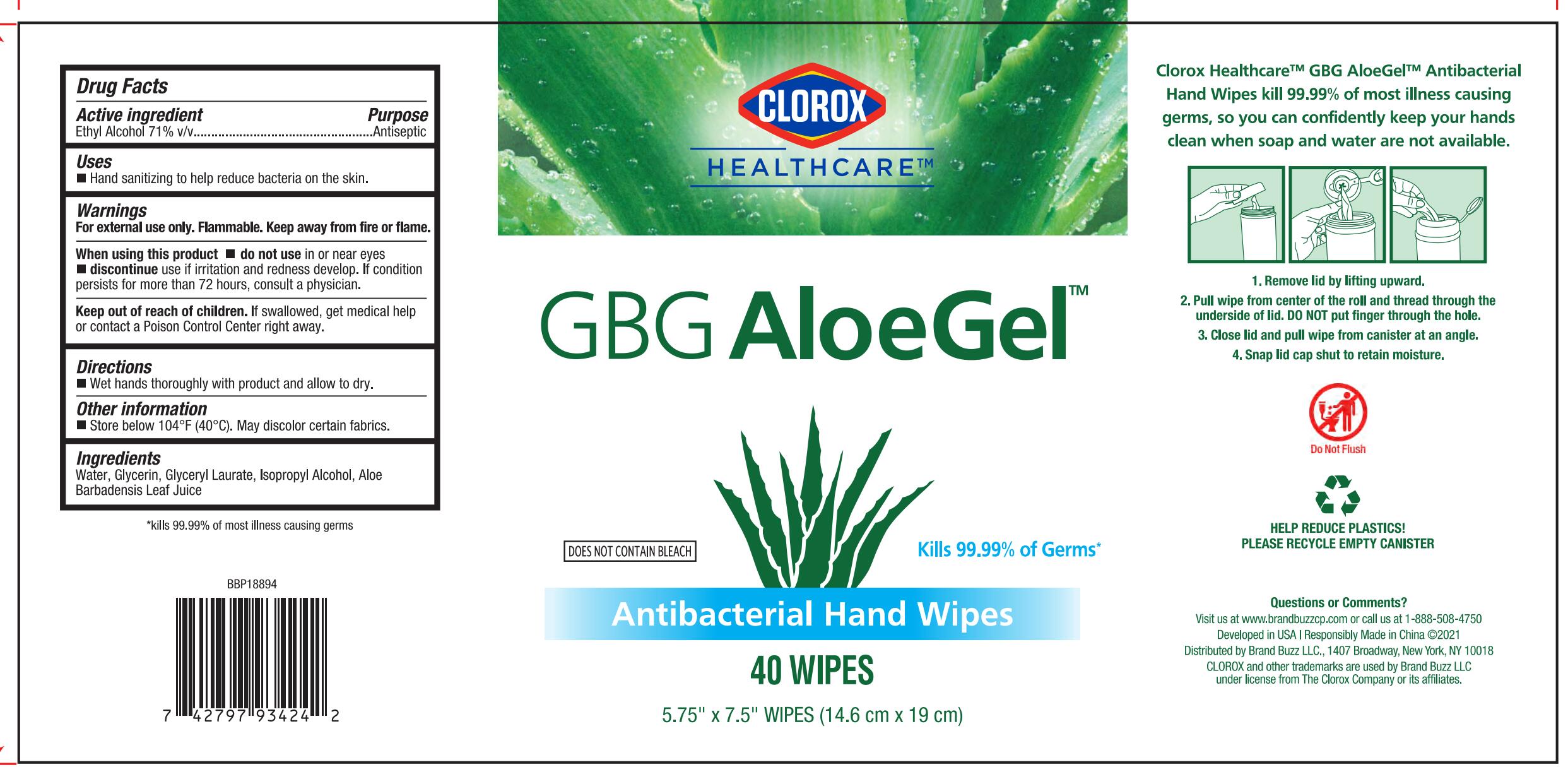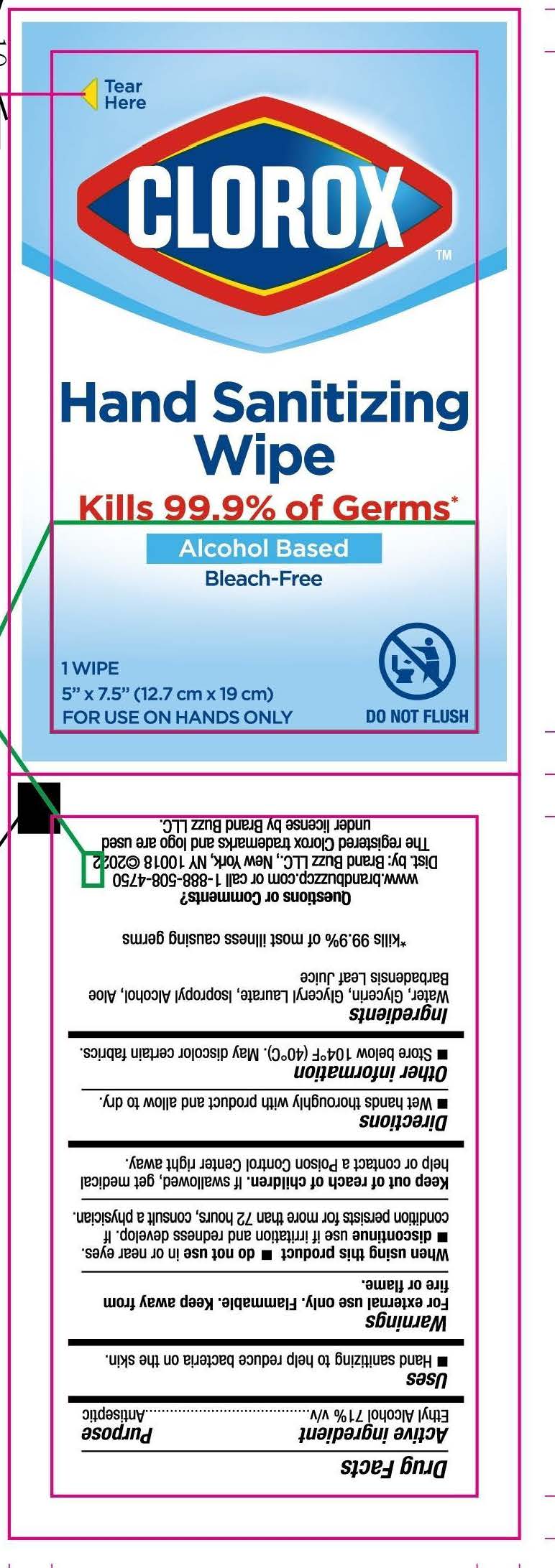 DRUG LABEL: Clorox Healthcare GBG AloeGel
NDC: 69540-0037 | Form: CLOTH
Manufacturer: Brand Buzz LLC
Category: otc | Type: HUMAN OTC DRUG LABEL
Date: 20250303

ACTIVE INGREDIENTS: ALCOHOL 0.71 mL/1 mL
INACTIVE INGREDIENTS: WATER; GLYCERIN; GLYCERYL LAURATE; ALOE VERA LEAF; ISOPROPYL ALCOHOL

Clorox Healtcare™ Antibacterial Hand Wipes

Active ingredient

Ethyl Alcohol 71% v/v

Purpose

Antiseptic

Uses

- Hand sanitizing to help reduce bacteria on the skin.

Warnings

For external use only. Keep away from fire or flame.

When using this product

- Do not use in or near the eyes.
- Discontinue use if irritation and redness develop. If condition persists for more than 72 hours, consult a physician.

Keep out of reach of children.

If swallowed, get medical help or contact a Poison Control Center right away

Directions

- Wet hands thoroughly with product and allow to dry.

Other Information

- Store below 104℉ (40℃). May discolor certain fabrics.

Ingredients

Water, Glycerin, Glyceral Laurate, Isopropyl Alcohol, Aloe Barbadensis Leaf Juice

Questions of Comments?

Visit us at www.brandbuzzcp.com or call us at 1-888-508-4750

PACKAGE LABEL

CLOROX HEALTHCARE™

GBG AloeGel™

Kills 99.99% Germs*

DOES NOT CONTAIN BLEACH

Antibacterial Hand Wipes

Clorox Healthcare™ GBG AloeGel™ Antibacterial Hand Wipes kill 99.99% of most illness causing germs, so you can confidently keep your hands clean when soap and water are not available

Wipe dimensions: 5.75in. x 7.5in. (14.6 cm x 19 cm)

1. Remove lid by lifting upward.
2. Pull wipe from center of the roll and thread through the underside of lid. DO NOT put finger through the hole.
3. Close lid and pull wipe from canister at an angle.
4. Snap lid cap shut to retain moisture.

Developed in USA | Responsibly Made in China ©2021

Distributed by Brand Buzz LLC., 1407 Broadway, New York, NY 10018

CLOROX and other trademarks are used by Brand Buzz LLC under license from The Clorox Company or its affiliates.

*kills 99.99% of most illness causing germs

1x100 Wipes

20 Wipes

40 Wipes

100 Wipes

270 Wipes

CLOROX™

Hand Sanitizing Wipe

Kills 99.99% Germs*

Alcohol-Based

Bleach-Free

For use on hands only

1 Wipe: 5in. x 7.5in. (12.7cm x 19cm)

*kills 99.99% of most illness causing germs

Dist. by: Brand Buzz LLC., 1407 Broadway, New York, NY 10018

The registered Clorox trademarks and logo are used under license by Brand Buzz LLC.

1x40 Wipes